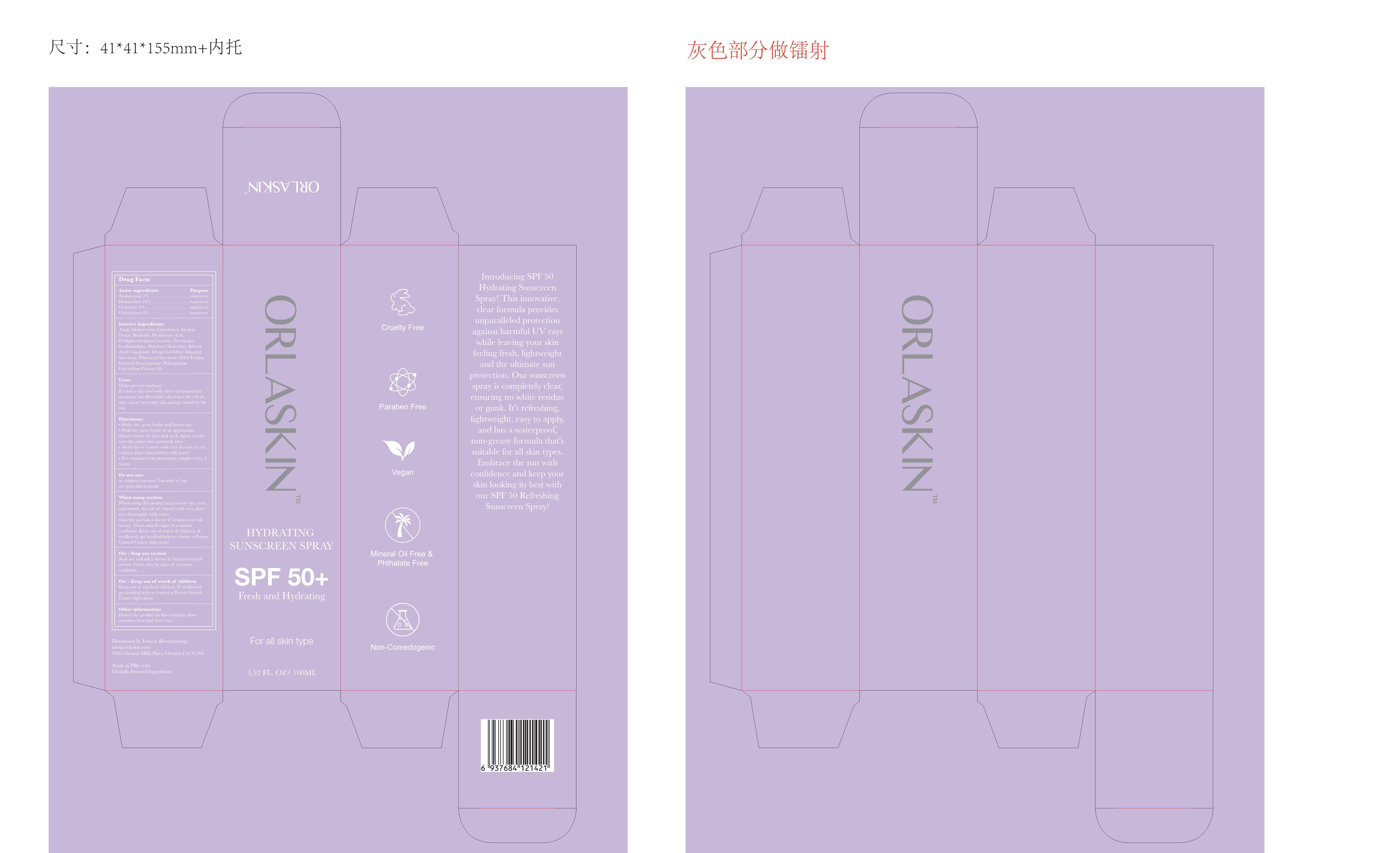 DRUG LABEL: HYDRATING SUNSCREEN
NDC: 84356-001 | Form: SPRAY
Manufacturer: Guangzhou Yapeng Refinement Chemical Co., Ltd.
Category: otc | Type: HUMAN OTC DRUG LABEL
Date: 20260104

ACTIVE INGREDIENTS: AVOBENZONE 3 g/100 mL; OCTISALATE 5 g/100 mL; HOMOSALATE 10 g/100 mL; OCTOCRYLENE 8 g/100 mL
INACTIVE INGREDIENTS: KAKADU PLUM; AMMONIO METHACRYLATE COPOLYMER TYPE A; WATER; ALCOHOL; LEVOMENOL; HYALURONIC ACID; .ALPHA.-TOCOPHEROL ACETATE, DL-

84356-001

Active Ingredient(s)

Avobenzone 3%

Homosalate 10%

Octocrylene 8%

Octilsalate 5%

Purpose

sunscreen

Use

USES:
Helps prevent sunburn. If used as directed with other sun protection measures (see directions),
decreases the risk of skin cancer and early skin ageing caused by the sun.

Do not use

in children less than 2 months of age on open skin wounds.

When using this product keep out of eyes, ears, and mouth. In case of contact with
eyes, rinse eyes thoroughly with water. Stop use and ask a doctor if irritation or
rash occurs. These may be signs of a serious condition. Keep out of reach of
children. If swallowed, get medical help or contact a Poison Control Center right away.

Stop use and ask a doctor if irritation or rash occurs. These may be signs of a
serious condition.

Keep out of reach of children. If swallowed, get medical help or contact a Poison
Control C enter right away.

Directions

DIRECTION:
1.Shake the spray bottle well before use.

2.Hold the spray bottle at an appropriate distance from the face and neck. Spray evenly onto the entire face and neck area.

3.Avoid direct contact with eyes. In case of eye contact, rinse immediately with water.
4.For continued sun protection, reapply every 2 hours.

Other information

- Protect the product in this container from excessive heat and direct sun.

Inactive ingredients

Auqa, Methacrylate Copolymer, Alcohol Denat, Bisabolol, Hyaluronic Acid,

D- Alpha-tocopheryl acetate, Terminalia Ferdinandiana, Butyloctyl Salicylate,
Sebacic Acid Copolymer, Dicaprylyl Ether, Diheptyl Succinate, Disooctyl Succinate,
Ethyl Ferulat, IsononyI Isononanoate, Pelargonium Graveolens Flower Oil.